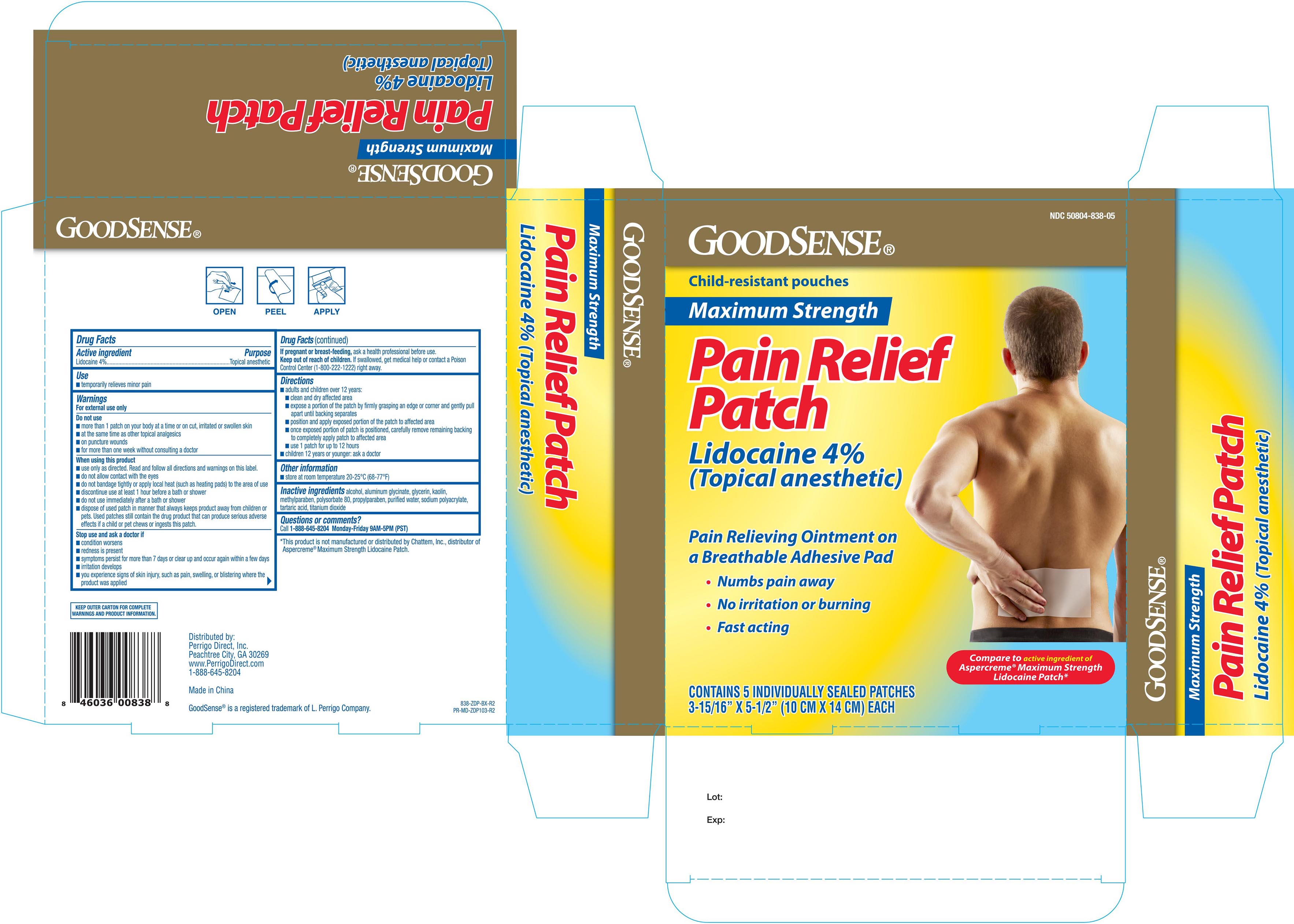 DRUG LABEL: GoodSense Pain Relief
NDC: 50804-838 | Form: PATCH
Manufacturer: Geiss, Destin & Dunn, Inc
Category: otc | Type: HUMAN OTC DRUG LABEL
Date: 20251028

ACTIVE INGREDIENTS: LIDOCAINE 40 mg/1 1
INACTIVE INGREDIENTS: POLYSORBATE 80; PROPYLPARABEN; ALCOHOL; DIHYDROXYALUMINUM AMINOACETATE ANHYDROUS; SODIUM POLYACRYLATE (8000 MW); TITANIUM DIOXIDE; WATER; KAOLIN; METHYLPARABEN

GoodSense Pain Relief Patch 5 ct. Lidocaine 4% ZDP 838

Active ingredient Purpose

Lidocaine 4%..................................................................Topical anesthetic.

Use

- temporarily relieves minor pain

Warnings

For external use only

Do not use

- more than 1 patch on your body at a time or on cut, irritated or swollen skin
- at the same time as other topical analgesics
- on puncture wounds
- for more than one week without consulting a doctor

When using this product

- use only as directed. Read and follow all directions and warnings on this label.
- do not allow contact with the eyes
- do not bandage tightly or apply local heat (such as heating pads) to the area of use
- discontinue use at least 1 hour before a bath or shower
- do not use immediately after a bath or shower
- dispose of used patch in matter that always keeps product away from children or pets. Used patches still contain the drug product that can produce serious adverse effects if a child or pet chews or ingests this patch

Stop use and ask a doctor if

- condition worsens
- redness is present
- symptoms persist for more than 7 days or clear up and occur again within a few days
- irritation develops
- you experience signs of skin injury, such as pain, swelling, or blistering where the product was applied

PREGNANCY OR BREAST FEEDING

If pregnant or breast-feeding, ask a health professional before use.

Keep out of reach of children. If swallowed, get medical help or contact a Poison Control Center (1-800-222-1222) right away.

Directions

- adults and children over 12 years:
- clean and dry affected area
- remove backing from patch by firmly grasping both ends and gently pulling until backing separates in middle
- carefully remove smaller portion of backing from patch and apply exposed portion of patch to affected area
- once exposed portion of patch is positioned, carefully remove remaining backing to completely apply patch to affected area
- use 1 patch for up to 12 hours
- children 12 years or younger: ask doctor

Other information

- store at room temperature 20-25°C (68-77°F)

Inactive ingredients

alcohol, aluminum glycinate, glycerin, kaolin, methylparaben, polysorbate 80, propylparaben, purified water, sodium polyacrylate, tartaric acid, titanium dioxide

DOSAGE AND ADMINISTRATION

Distributed by:

Geiss, Destin & Dunn, Inc.

Peachtree City, GA 30269

Made in China